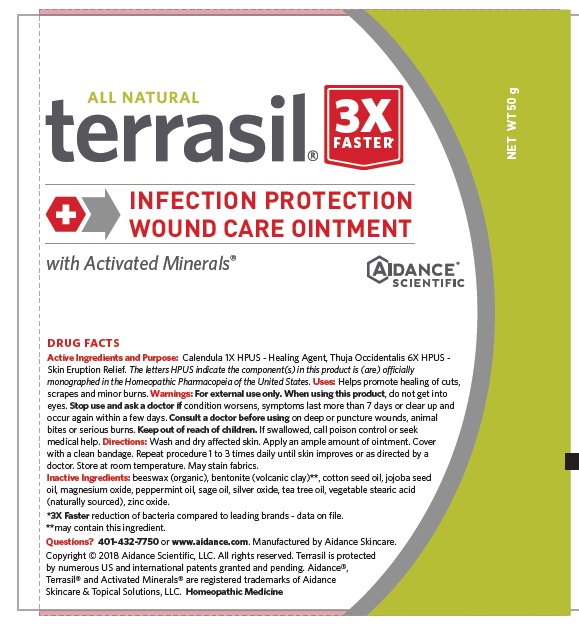 DRUG LABEL: terrasil INFECTION PROTECTION WOUND CARE
NDC: 24909-168 | Form: OINTMENT
Manufacturer: Aidance Skincare & Topical Solutions, LLC
Category: homeopathic | Type: HUMAN OTC DRUG LABEL
Date: 20240524

ACTIVE INGREDIENTS: CALENDULA OFFICINALIS FLOWER 1 [hp_X]/50 g; THUJA OCCIDENTALIS WHOLE 6 [hp_X]/50 g
INACTIVE INGREDIENTS: WHITE WAX; BENTONITE; COTTONSEED OIL; JOJOBA OIL; MAGNESIUM OXIDE; PEPPERMINT OIL; SAGE OIL; SILVER OXIDE; TEA TREE OIL; STEARIC ACID; ZINC OXIDE

24909-168 terrasil Infection Protection Wound Care Ointment

Active Ingredients

Calendula 1X HPUS, Thuja occidentalis 6X HPUS

The letters HPUS indicate the component(s) in this product is (are) officially monographed in the Homeopathic Pharmacopeia of the United States

Purpose

Calendula - Healing Agent, Thuja - Skin Eruption Relief

Uses

Helps promote healing of cuts, scrapes and minor burns.

Warnings

For external use only. When using this product, do not get into eyes. Stop use and ask a doctor ifcondition worsens, symptoms last more than 7 days or clear up and occur again within a few days. Consult a doctor before usingon deep or puncture wounds, animal bites or serious burns.

Keep out of reach of children.

If swallowed, call poison control or seek medical help

Directions

Wash and dry affected skin. Apply an ample amount of ointment. Cover

with a clean bandage. Repeat procedure 1 to 3 times daily until skin improves or as directed by a

doctor. Store at room temperature. May stain fabrics.

Inactive Ingredients

beeswax (organic), bentonite (volcanic clay)**, cotton seed oil, jojoba seed oil, magnesium oxide, peppermint oil, sage oil, silver oxide, tea tree oil, vegetable stearic acid (naturally sourced), zinc oxide.

**may contain this ingredient.

PRINCIPAL DISPLAY PANEL - 50g Tube

terrasil

INFECTION PROTECTION WOUND CARE OINTMENT